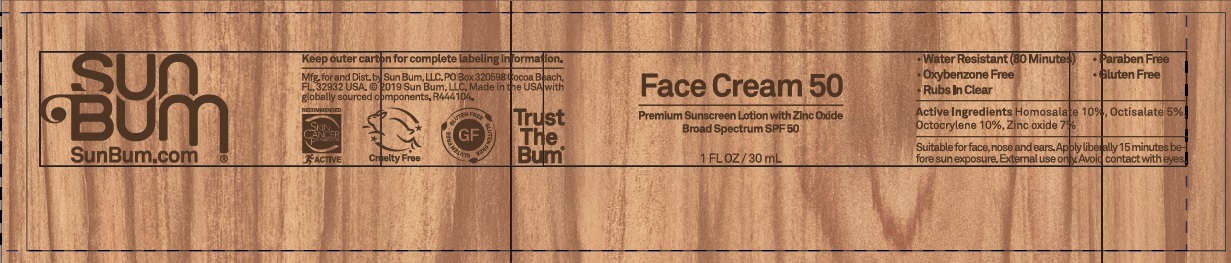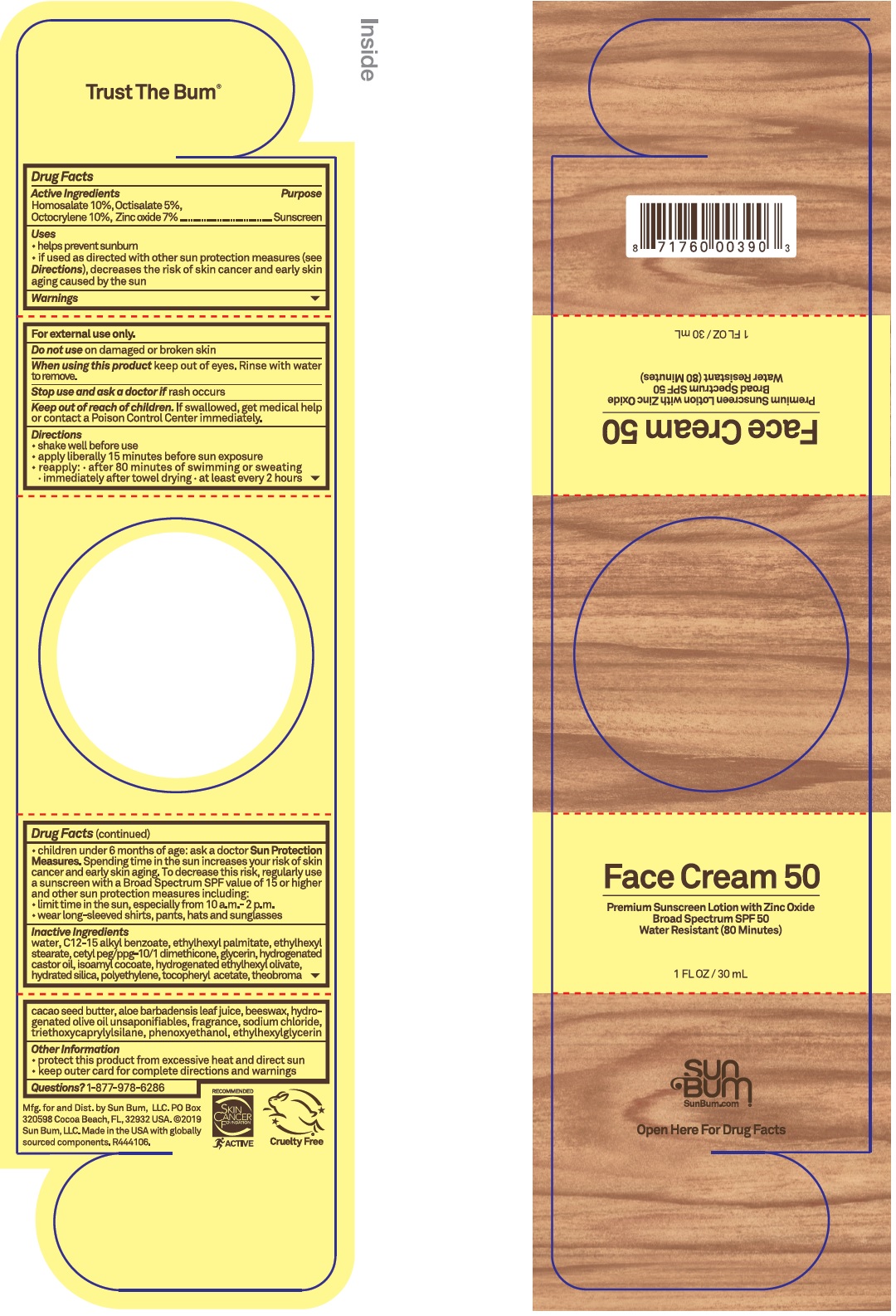 DRUG LABEL: Face Cream 50
NDC: 69039-661 | Form: CREAM
Manufacturer: Sun Bum LLC
Category: otc | Type: HUMAN OTC DRUG LABEL
Date: 20230119

ACTIVE INGREDIENTS: HOMOSALATE 100 mg/1 mL; OCTISALATE 50 mg/1 mL; OCTOCRYLENE 100 mg/1 mL; ZINC OXIDE 70 mg/1 mL
INACTIVE INGREDIENTS: WATER; ALKYL (C12-15) BENZOATE; ETHYLHEXYL PALMITATE; ETHYLHEXYL STEARATE; GLYCERIN; HYDROGENATED CASTOR OIL; ISOAMYL COCOATE; HYDRATED SILICA; HIGH DENSITY POLYETHYLENE; .ALPHA.-TOCOPHEROL ACETATE; ALOE VERA LEAF; YELLOW WAX; HYDROGENATED OLIVE OIL UNSAPONIFIABLES; SODIUM CHLORIDE; TRIETHOXYCAPRYLYLSILANE; PHENOXYETHANOL; ETHYLHEXYLGLYCERIN

Face Cream 50

Active Ingredients

Homosalate 10%, Octisalate 5%

Octocrylene 10%, Zinc oxide 7%

Purpose

Sunscreen

Uses

- helps prevent sunburn
- if used as directed with other sun protection measures (see Directions), decreases the risk of skin cancer and early skin aging caused by the sun

Warnings

For external use only.

Do not use

on damaged or broken skin

When using this product

keep out of eyes. Rinse with water to remove.

Stop use and ask a doctor if

rash occurs

Keep out of reach of children.

If swallowed, get medical help or contact a Poison Control Center immediately.

Directions

• shake well before use

• apply liberally 15 minutes before sun exposure

• reapply: • after 80 minutes of swimming or sweating

• immediately after towel drying • at least every 2 hours

• children under 6 months of age: ask a doctor Sun Protection Measures. Spending time in the sun increases your risk of skin cancer and early skin aging. To decrease this risk, regularly use a sunscreen with a Broad Spectrum SPF value of 15 or higher and other sun protection measures including:

• limit time in the sun, especially from 10 a.m. - 2 p.m.

• wear long-sleeved shirts, pants, hats and sunglasses

Inactive Ingredients

water, C12-15 alkyl benzoate, ethylhexyl palmitate, ethylhexyl stearate, cetyl peg/ppg-10/1 dimethicone, glycerin, hydrogenated castor oil, isoamyl cocoate, hydrogenated ethylhexyl olivate, hydrated silica, polyethylene, tocopheryl acetate, theobroma cacao seed butter, aloe barbadensis leaf juice, beeswax, hydrogenated olive oil unsaponifiables, fragrance, sodium chloride, triethoxycaprylysilane, phenoxyethanol, ethylhexylglycerin

Other Information

• protect this product from excessive heat and direct sun
• keep outer card for complete directions and warnings

Questions?

1-877-978-6286